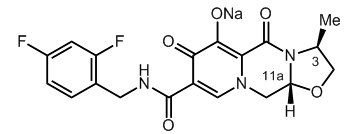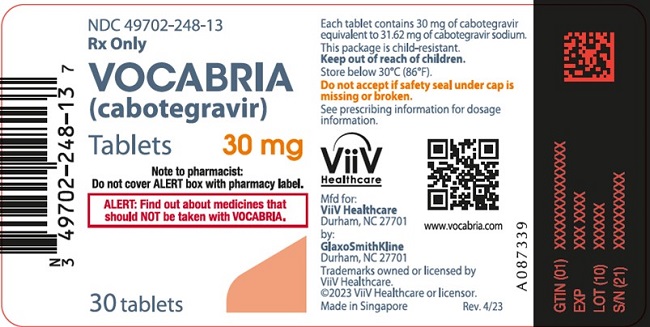 DRUG LABEL: Vocabria
NDC: 49702-248 | Form: TABLET, FILM COATED
Manufacturer: ViiV Healthcare Company
Category: prescription | Type: HUMAN PRESCRIPTION DRUG LABEL
Date: 20250411

ACTIVE INGREDIENTS: CABOTEGRAVIR SODIUM 30 mg/1 1
INACTIVE INGREDIENTS: HYPROMELLOSE, UNSPECIFIED; LACTOSE MONOHYDRATE; MAGNESIUM STEARATE; MICROCRYSTALLINE CELLULOSE; SODIUM STARCH GLYCOLATE TYPE A CORN; POLYETHYLENE GLYCOL, UNSPECIFIED; TITANIUM DIOXIDE

HIGHLIGHTS OF PRESCRIBING INFORMATION

These highlights do not include all the information needed to use VOCABRIA safely and effectively. See full prescribing information for VOCABRIA.
VOCABRIA (cabotegravir) tablets, for oral use
Initial U.S. Approval: 2021

RECENT MAJOR CHANGES

Warnings and Precautions, Hypersensitivity Reactions (5.2) | 4/2025

1 INDICATIONS AND USAGE

HIV-1 Treatment: VOCABRIA is an HIV-1 integrase strand transfer inhibitor (INSTI) indicated in combination with EDURANT (rilpivirine) for short-term treatment of HIV-1 infection in adults and adolescents 12 years of age and older and weighing at least 35 kg who are virologically suppressed (HIV-1 RNA <50 copies/mL) on a stable antiretroviral regimen with no history of treatment failure and with no known or suspected resistance to either cabotegravir or rilpivirine. (1.1)

HIV-1 Pre-Exposure Prophylaxis: VOCABRIA is indicated for short-term pre-exposure prophylaxis (PrEP) to reduce the risk of sexually acquired HIV-1 infection in adults and adolescents weighing at least 35 kg who are at risk for HIV-1 acquisition. Individuals must have a negative HIV-1 test prior to initiating VOCABRIA for HIV-1 PrEP. (1.2)

VOCABRIA may be used as:

- oral lead-in to assess the tolerability of cabotegravir prior to administration of CABENUVA (cabotegravir extended-release injectable suspension; rilpivirine extended-release injectable suspension) for HIV-1 treatment or APRETUDE (cabotegravir extended-release injectable suspension) for HIV-1 PrEP. (1.1, 1.2)
- oral therapy for patients who will miss planned injection dosing with CABENUVA for HIV-1 treatment or APRETUDE for HIV-1 PrEP. (1.1, 1.2)

2 DOSAGE AND ADMINISTRATION

- One tablet of VOCABRIA 30 mg taken orally once daily in combination with 1 tablet of EDURANT 25 mg taken orally once daily with a meal:
  - for approximately 1 month if oral lead-in is used for HIV-1 treatment. (2.1)
  - for up to 2 months to replace up to 2 consecutive missed monthly injections of CABENUVA (2.2)
Refer to 2.1 for dosing recommendations for missed injections. (2.1)
- HIV-1 Screening: Screen all individuals for HIV-1 infection prior to initiating VOCABRIA and APRETUDE for HIV-1 PrEP and at least once every 3 months while taking APRETUDE. (2.2)
- One tablet of VOCABRIA 30 mg taken orally once daily for approximately 1 month if oral lead-in is used for HIV-1 PrEP. Refer to 2.2 for dosing recommendations for missed injections. (2.2)

3 DOSAGE FORMS AND STRENGTHS

Tablets: 30 mg (3)

4 CONTRAINDICATIONS

- Previous hypersensitivity reaction to cabotegravir. (4)
- Coadministration with carbamazepine, oxcarbazepine, phenobarbital, phenytoin, rifampin, and rifapentine. (4)
- Positive HIV-1 status for HIV-1 PrEP. (4)

5 WARNINGS AND PRECAUTIONS

- HIV-1 PrEP: Comprehensive management to reduce the risk of HIV-1 acquisition. (5.1)
- Serious or severe hypersensitivity reactions have been reported with cabotegravir and include Stevens-Johnson syndrome (SJS)/toxic epidermal necrolysis (TEN). Discontinue VOCABRIA immediately if signs or symptoms of hypersensitivity reactions develop. (5.2)
- Hepatotoxicity has been reported in patients receiving cabotegravir. Monitoring of liver chemistries is recommended when VOCABRIA is used for HIV-1 treatment. Clinical and laboratory monitoring should be considered when VOCABRIA is used for HIV-1 PrEP. Discontinue VOCABRIA if hepatotoxicity is suspected. (5.3)
- Depressive disorders have been reported with VOCABRIA when used with EDURANT for HIV-1 treatment. Prompt evaluation is recommended for depressive symptoms. (5.4)
- Risks Associated with Combination Treatment: Review the prescribing information for EDURANT for information on rilpivirine prior to initiation of VOCABRIA in combination with EDURANT. (5.6)

6 ADVERSE REACTIONS

- In patients with HIV-1, the most common adverse reactions observed in at least 3 participants receiving VOCABRIA were fatigue, headache, diarrhea, nausea, dizziness, abnormal dreams, anxiety, insomnia, abdominal discomfort, abdominal distension, and asthenia. (6.1)
- In individuals without HIV-1 receiving VOCABRIA, the most common adverse reactions reported in ≥1% were headache, diarrhea, nausea, dizziness, upper respiratory tract infection, somnolence, fatigue, abnormal dreams, and abdominal pain. (6.1)

To report SUSPECTED ADVERSE REACTIONS, contact ViiV Healthcare at 1-877-844-8872 or FDA at 1-800-FDA-1088 or www.fda.gov/medwatch.

7 DRUG INTERACTIONS

- Refer to the full prescribing information for important drug interactions with VOCABRIA. (4, 5.5, 7)
- VOCABRIA in combination with EDURANT is a complete regimen for HIV-1 treatment. Coadministration with other antiretroviral medications for PrEP is not recommended. (7.1)
- Drugs that induce uridine diphosphate glucuronosyltransferase (UGT)1A1 may decrease the plasma concentrations of cabotegravir. (4, 7.2, 7.3)

FULL PRESCRIBING INFORMATION

1 INDICATIONS AND USAGE

1.1 Treatment of HIV-1 Infection

VOCABRIA is indicated in combination with EDURANT (rilpivirine) tablets for short-term treatment of HIV-1 infection in adults and adolescents 12 years of age and older and weighing at least 35 kg who are virologically suppressed (HIV-1 RNA <50 copies/mL) on a stable antiretroviral regimen with no history of treatment failure and with no known or suspected resistance to either cabotegravir or rilpivirine, for use as [see Microbiology (12.4), Clinical Studies (14.1)]:

- oral lead-in to assess the tolerability of cabotegravir prior to administration of cabotegravir extended-release injectable suspension, a component of CABENUVA (cabotegravir extended-release injectable suspension; rilpivirine extended-release injectable suspension).
- oral therapy for patients who will miss planned injection dosing with CABENUVA.

1.2 HIV-1 Pre-Exposure Prophylaxis

VOCABRIA is indicated for short-term pre-exposure prophylaxis (PrEP) to reduce the risk of sexually acquired HIV-1 infection in adults and adolescents weighing at least 35 kg who are at risk for HIV-1 acquisition. Individuals must have a negative HIV-1 test prior to initiating VOCABRIA for HIV-1 PrEP. VOCABRIA may be used as [see Dosage and Administration (2.2), Contraindications (4), Warnings and Precautions (5.1), Clinical Studies (14.2)]:

- oral lead-in to assess the tolerability of cabotegravir prior to administration of APRETUDE (cabotegravir extended-release injectable suspension).
- oral PrEP for patients who will miss planned injection dosing with APRETUDE.

2 DOSAGE AND ADMINISTRATION

2.1 Treatment of HIV-1 Infection in Adults and Adolescents 12 Years of Age and Older and Weighing at Least 35 kg

Oral Lead-In Dosing to Assess Tolerability of Cabotegravir

Consult the prescribing information for CABENUVA (cabotegravir extended-release injectable suspension; rilpivirine extended-release injectable suspension) before initiating VOCABRIA to ensure therapy with CABENUVA is appropriate. See full prescribing information for CABENUVA.

Oral lead-in may be used to assess the tolerability of cabotegravir prior to the initiation of CABENUVA. The recommended oral lead-in daily dose is one 30-mg tablet of VOCABRIA with one 25-mg tablet of EDURANT for approximately 1 month (at least 28 days). The last oral dose should be taken on the same day injections with CABENUVA are started.

Take VOCABRIA once daily with EDURANT at approximately the same time each day with a meal [see Clinical Pharmacology (12.3)].

Because VOCABRIA is indicated in combination with EDURANT tablets, the prescribing information for EDURANT should also be consulted.

Recommended Oral Dosing to Replace Planned Missed Injections of CABENUVA

Planned Missed Injections for Patients on the Monthly Dosing Schedule: If a patient plans to miss a monthly scheduled injection of CABENUVA by more than 7 days, take daily oral therapy for up to 2 months to replace missed injection visits. For oral therapy with VOCABRIA and EDURANT, the recommended oral daily dose is one 30‑mg tablet of VOCABRIA and one 25-mg tablet of EDURANT. Take VOCABRIA with EDURANT at approximately the same time each day with a meal.

The first dose of oral therapy should be taken 1 month (+/-7 days) after the last injection dose of CABENUVA and continued until the day injection dosing is restarted. For oral therapy with VOCABRIA and EDURANT of durations greater than 2 months, an alternative oral regimen is recommended. See full prescribing information for CABENUVA to resume monthly injection dosing.

Planned Missed Injections for Patients on the Every-2-Month Dosing Schedule: If a patient plans to miss a scheduled every-2-month injection of CABENUVA by more than 7 days, take daily oral therapy for up to 2 months to replace 1 missed scheduled every-2-month injection. For oral therapy with VOCABRIA and EDURANT of durations greater than 2 months, the recommended oral daily dose is one 30-mg tablet of VOCABRIA and one 25-mg tablet of EDURANT. Take VOCABRIA with EDURANT at approximately the same time each day with a meal.

The first dose of oral therapy should be taken approximately 2 months after the last injection dose of CABENUVA and continued until the day injection dosing is restarted. For oral therapy with VOCABRIA and EDURANT of durations greater than 2 months, an alternative oral regimen is recommended. See full prescribing information for CABENUVA to resume every-2-month injection dosing.

2.2 HIV-1 Pre-Exposure Prophylaxis in Adults and Adolescents Weighing at Least 35 kg

HIV-1 Screening for Individuals for HIV-1 Pre-Exposure Prophylaxis

Individuals must be tested for HIV-1 infection prior to initiating VOCABRIA and APRETUDE for HIV-1 PrEP, and with each subsequent injection of APRETUDE, using a test approved or cleared by the FDA for the diagnosis of acute or primary HIV-1 infection. If an antigen/antibody-specific test is used and provides negative results, then such negative results should be confirmed using an RNA-specific assay, even if the results of the RNA-assay are available after VOCABRIA or APRETUDE administration [see Contraindications (4), Warnings and Precautions (5.1)].

Oral Lead-In Dosing to Assess Tolerability of Cabotegravir for HIV-1 Pre-Exposure Prophylaxis

Consult the prescribing information for APRETUDE before initiating VOCABRIA to ensure use of APRETUDE is appropriate. See full prescribing information for APRETUDE.

Oral lead-in may be used to assess the tolerability of cabotegravir prior to the initiation of APRETUDE. The recommended oral daily dose is one 30-mg tablet of VOCABRIA for approximately 1 month (at least 28 days). Following oral lead-in, start initiation injection of APRETUDE on the last day of oral lead-in or within 3 days.

Oral Dosing to Replace a Planned Missed Injection of APRETUDE (One Every-2-Month Injection)

If an individual plans to miss a scheduled injection of APRETUDE by more than 7 days, take daily oral VOCABRIA to replace one every-2-month injection visit. The recommended oral daily dose is one 30-mg tablet of VOCABRIA. The first dose of oral VOCABRIA should be taken approximately 2 months after the last injection dose of APRETUDE. Restart injection with APRETUDE on the day oral dosing completes or within 3 days. See full prescribing information for APRETUDE to resume every-2-month injection dosing.

3 DOSAGE FORMS AND STRENGTHS

Tablets: 30 mg.

4 CONTRAINDICATIONS

Treatment of HIV-1 Infection

VOCABRIA is contraindicated in patients:

- with previous hypersensitivity reaction to cabotegravir [see Warnings and Precautions (5.2)].
- receiving the following coadministered drugs for which significant decreases in cabotegravir plasma concentrations may occur due to uridine diphosphate glucuronosyltransferase (UGT)1A1 enzyme induction, which may result in loss of virologic response [see Drug Interactions (7.2, 7.3), Clinical Pharmacology (12.3)]:
  - Anticonvulsants: Carbamazepine, oxcarbazepine, phenobarbital, phenytoin
  - Antimycobacterials: Rifampin, rifapentine

Prior to initiation of VOCABRIA, note that use of CABENUVA (cabotegravir extended-release injectable suspension; rilpivirine extended-release injectable suspension) with rifabutin is contraindicated.

Since VOCABRIA is taken in combination with EDURANT tablets, the prescribing information for EDURANT should be consulted for additional contraindications.

HIV-1 Pre-Exposure Prophylaxis

VOCABRIA is contraindicated in individuals:

- with unknown or positive HIV-1 status [see Warnings and Precautions (5.1)].
- with previous hypersensitivity reaction to cabotegravir [see Warnings and Precautions (5.2)].
- receiving the following coadministered drugs for which significant decreases in cabotegravir plasma concentrations may occur due to UGT1A1 enzyme induction, which may result in loss of efficacy [see Drug Interactions (7.2, 7.3), Clinical Pharmacology (12.3)]:
  - Anticonvulsants: Carbamazepine, oxcarbazepine, phenobarbital, phenytoin
  - Antimycobacterials: Rifampin, rifapentine

5 WARNINGS AND PRECAUTIONS

5.1 Comprehensive Management to Reduce the Risk of HIV-1 Infection When VOCABRIA is Used for HIV-1 Pre-Exposure Prophylaxis

Use of VOCABRIA for HIV-1 PrEP should be part of a comprehensive prevention strategy including adherence to the dosing schedule and safer sex practices, including condoms, to reduce the risk of sexually transmitted infections (STIs). VOCABRIA is not always effective in preventing HIV-1 acquisition [see Clinical Studies (14.2)]. The time from initiation of VOCABRIA for HIV-1 PrEP to maximal protection against HIV-1 infection is unknown.

Risk for HIV-1 acquisition includes behavioral, biological, or epidemiologic factors including, but not limited to, condomless sex, past or current STIs, self-identified HIV risk, having sexual partners of unknown HIV-1 viremic status, or sexual activity in a high prevalence area or network.

Counsel individuals on the use of other prevention measures (e.g., consistent and correct condom use; knowledge of partner(s)’ HIV-1 status, including viral suppression status; regular testing for STIs that can facilitate HIV-1 transmission). Inform individuals about and support their efforts in reducing sexual risk behavior.

VOCABRIA for HIV-1 PrEP to reduce the risk of acquiring HIV-1 should be used only in individuals confirmed to be HIV-1 negative [see Contraindications (4)]. HIV-1 resistance substitutions may emerge in individuals with undiagnosed HIV-1 infection who are taking only VOCABRIA, because VOCABRIA alone does not constitute a complete regimen for HIV-1 treatment [see Microbiology (12.4)]; therefore, care should be taken to minimize the risk of initiating or continuing VOCABRIA before confirming the individual is HIV-1 negative.

- Prior to initiating VOCABRIA for HIV-1 PrEP, ask seronegative individuals about recent (in past month) potential exposure events (e.g., condomless sex or condom breaking during sex with a partner of unknown HIV-1 status or unknown viremic status, a recent STI), and evaluate for current or recent signs or symptoms consistent with acute HIV-1 infection (e.g., fever, fatigue, myalgia, skin rash).
- If recent (<1 month) exposures to HIV-1 are suspected or clinical symptoms consistent with acute HIV-1 infection are present, use a test approved or cleared by the FDA as an aid in the diagnosis of acute or primary HIV-1 infection. Testing should be repeated prior to each injection of APRETUDE and upon diagnosis of any other STIs [see Dosage and Administration (2.2)].
- If an HIV-1 test indicates possible HIV-1 infection, or if symptoms consistent with acute HIV-1 infection develop following an exposure event, additional HIV testing to determine HIV status is needed. If an individual has confirmed HIV-1 infection, then the individual must be transitioned to a complete HIV-1 treatment regimen.

Counsel individuals without HIV-1 to strictly adhere to the recommended dosing schedule for VOCABRIA in order to reduce the risk of HIV-1 acquisition and the potential development of resistance [see Dosage and Administration (2.2), Microbiology (12.4)]. Some individuals, such as adolescents, may benefit from frequent visits and counseling to support adherence to the dosing schedule [see Use in Specific Populations (8.4), Microbiology (12.4), Clinical Studies (14.2)].

5.2 Hypersensitivity Reactions

Serious or severe hypersensitivity reactions have been reported with cabotegravir and include Stevens-Johnson syndrome (SJS)/toxic epidermal necrolysis (TEN) [see Adverse Reactions (6.2)]. Administration of oral lead-in dosing was used in clinical studies to help identify participants who may be at risk of a hypersensitivity reaction. Remain vigilant and discontinue VOCABRIA if a hypersensitivity reaction is suspected [see Dosage and Administration (2.2), Contraindications (4), Adverse Reactions (6)].

Discontinue VOCABRIA immediately if signs or symptoms of hypersensitivity reactions develop (including, but not limited to, severe rash, or rash accompanied by fever, general malaise, fatigue, muscle or joint aches, blisters, mucosal involvement [oral blisters or lesions], conjunctivitis, facial edema, hepatitis, eosinophilia, angioedema, difficulty breathing). Clinical status, including liver transaminases, should be monitored and appropriate therapy initiated.

5.3 Hepatotoxicity

Hepatotoxicity has been reported in a limited number of patients receiving cabotegravir with or without known pre-existing hepatic disease or identifiable risk factors [see Adverse Reactions (6.1)].

When VOCABRIA is Used for Treatment HIV-1 Infection

Patients with underlying liver disease or marked elevations in transaminases prior to treatment with VOCABRIA may be at increased risk for worsening or development of transaminase elevations.

Monitoring of liver chemistries is recommended and treatment with VOCABRIA should be discontinued if hepatotoxicity is suspected.

When VOCABRIA is Used for HIV-1 Pre-Exposure Prophylaxis

Clinical and laboratory monitoring should be considered and VOCABRIA should be discontinued if hepatotoxicity is suspected, and individuals managed as clinically indicated.

5.4 Depressive Disorders

When VOCABRIA is Used for Treatment HIV-1 Infection

Depressive disorders (including depressed mood, depression, mood altered, mood swings, suicidal ideation/suicide attempt) have been reported with VOCABRIA when used with EDURANT for treatment of HIV-1 infection [see Adverse Reactions (6.1)]. Promptly evaluate patients with depressive symptoms to assess whether the symptoms are related to VOCABRIA and to determine whether the risks of continued therapy outweigh the benefits.

When VOCABRIA is Used for HIV-1 Pre-Exposure Prophylaxis

Depressive disorders (including depression, depressed mood, persistent depressive disorder, suicidal ideation/suicide attempt) have been reported with VOCABRIA [see Adverse Reactions (6.1)]. Promptly evaluate individuals with depressive symptoms to assess whether the symptoms are related to VOCABRIA and to determine whether the risks of continued therapy outweigh the benefits.

5.5 Risk of Adverse Reactions, Loss of Efficacy, or Reduced Concentration Due to Drug Interactions

The concomitant use of VOCABRIA and other drugs may result in known or potentially significant drug interactions, some of which may lead to adverse events, loss of efficacy from VOCABRIA when used for treatment of HIV-1 infection or HIV-1 PrEP, and possible development of viral resistance [see Contraindications (4), Drug Interactions (7.2, 7.3)].

See Table 1 for steps to prevent or manage these possible and known significant drug interactions, including dosing recommendations. Consider the potential for drug interactions prior to and during use of VOCABRIA; review concomitant medications during use of VOCABRIA [see Drug Interactions (7.3)].

5.6 Risks Associated with Combination Treatment

VOCABRIA is indicated for use in combination with EDURANT (rilpivirine) for treatment of HIV-1 infection [see Indications and Usage (1.1), Dosage and Administration (2.1)]. Review the prescribing information for EDURANT for information on rilpivirine prior to initiation of VOCABRIA in combination with EDURANT.

6 ADVERSE REACTIONS

The following adverse reactions are described below and in other sections of the labeling:

- Hypersensitivity reactions [see Warnings and Precautions (5.2)]
- Hepatotoxicity [see Warnings and Precautions (5.3)]
- Depressive disorders [see Warnings and Precautions (5.4)]

6.1 Clinical Trials Experience

Because clinical trials are conducted under widely varying conditions, adverse reaction rates observed in the clinical trials of a drug cannot be directly compared with rates in the clinical trials of another drug and may not reflect rates observed in practice. See full prescribing information for CABENUVA (cabotegravir extended-release injectable suspension; rilpivirine extended-release injectable suspension) for additional safety information. Since VOCABRIA is taken in combination with EDURANT tablets, the prescribing information for EDURANT (rilpivirine) should be consulted for relevant information on rilpivirine.

Adverse Reactions of VOCABRIA in Clinical Trials for the Treatment of HIV-1 Infection

Clinical Trials Experience in Adults: The safety assessment of VOCABRIA for oral lead-in therapy prior to therapy with CABENUVA is based on the analysis of 48-week data from virologically suppressed participants with HIV-1 infection in 3 international, multicenter, open-label trials, where 590 of 1,182 participants received oral lead-in within the pivotal trials FLAIR and ATLAS (pooled analysis) and 655 of 1,045 participants received oral lead-in within ATLAS-2M [see Clinical Studies (14.1)].

Adverse reactions were reported following exposure to VOCABRIA tablets and EDURANT tablets administered in combination as oral lead-in therapy (median time exposure: 5.3 weeks). Adverse reactions included those attributable to the oral formulation of cabotegravir and rilpivirine administered as a combination regimen. Refer to the prescribing information for EDURANT for other adverse reactions associated with oral rilpivirine.

The most common adverse reactions during the oral lead-in period in the pooled analyses of FLAIR and ATLAS at Week 48 were headache, nausea, abnormal dreams, anxiety, and insomnia, all of which occurred in at least 3 participants with an incidence ≤1%. The most common adverse reactions during the oral lead-in period for ATLAS-2M were fatigue, diarrhea, headache, nausea, dizziness, abdominal discomfort, abdominal distension, insomnia, and asthenia, all of which occurred in at least 3 participants across both arms, with an incidence ≤2%.

During the oral lead-in period for FLAIR and ATLAS, 6 (1%) participants discontinued due to adverse events, including asthenia, myalgia, depression suicidal, and headache. During the oral lead-in period for ATLAS-2M, 4 (<1%) participants discontinued due to adverse events, including asthenia, skin lesion, fatigue, transaminases increased, and depression.

In the extension phase of the FLAIR study at Week 124, the overall safety profile was consistent with that observed at Week 48 and when injection therapy with CABENUVA was initiated directly without the oral lead-in phase.

Clinical Trial Experience in Adolescents: Based on data from the Week 24 analysis of the MOCHA study in 144 adolescents (aged 12 to younger than 18 years and weighing ≥35 kg), the safety profile of oral cabotegravir and oral rilpivirine administered in combination during the oral lead-in period in adolescents was consistent with the safety profile established with cabotegravir plus rilpivirine in adults.

Adverse Reactions of VOCABRIA in Clinical Trials for HIV-1 Pre-Exposure Prophylaxis

Clinical Trial Experience in Adults: In trial HPTN 083, adverse reactions were reported while participants were on blinded study product following exposure to VOCABRIA tablets as oral lead-in for HIV-1 PrEP (median time exposure: 4.1 weeks). The most common adverse reactions reported at ≥1% during the oral lead-in period were diarrhea (4% and 4%), nausea (3% and 5%), dizziness (2% and 2%), headache (2% and 2%), fatigue (1% and 2%), and abnormal dreams (1% and 2%) for VOCABRIA and TRUVADA (emtricitabine and tenofovir disoproxil fumarate), respectively. During the oral lead-in period, 24 (1%) participants receiving VOCABRIA discontinued due to adverse events, including increased alanine aminotransferase, increased aspartate aminotransferase, suicide attempt, and dizziness, which were observed in ≥2 participants.

In Trial HPTN 084, adverse reactions were reported while participants were on blinded study product following exposure to VOCABRIA tablets as oral lead-in for HIV-1 PrEP (median time exposure: 4.1 weeks). The most common adverse reactions reported at ≥1% during the oral lead-in period were headache (6% and 7%), nausea (3% and 7%), dizziness (3% and 4%), diarrhea (2% and 4%), upper respiratory tract infection (2% and 2%), somnolence (2% and 1%), fatigue (1% and 2%), abdominal pain (1% and 1%), vomiting (<1% and 3%), decreased appetite (<1% and 2%), and pruritus (<1% and 1%) for VOCABRIA and TRUVADA, respectively. During the oral lead-in period, 4 (<1%) participants receiving VOCABRIA discontinued due to adverse events of increased alanine aminotransferase (n = 3) and sleep disorders (n = 1).

Clinical Trials Experience in Adolescents: In adolescents receiving VOCABRIA for HIV-1 PrEP, the safety data were comparable to the safety data reported in adults receiving VOCABRIA for HIV-1 PrEP [see Use in Specific Populations (8.4)].

Less Common Adverse Reactions

The following select adverse reactions (regardless of severity) occurred in <1% of participants receiving VOCABRIA in clinical trials for the treatment of HIV-1 infection or for HIV-1 PrEP.

Psychiatric Disorders: Suicidal ideation, and suicide attempt (these events were observed primarily in participants with a pre‑existing history of depression or other psychiatric illness).

6.2 Postmarketing Experience

The following adverse reactions have been identified during postmarketing use of VOCABRIA or cabotegravir-containing regimens. Because these reactions are reported voluntarily from a population of uncertain size, it is not always possible to reliably estimate their frequency or establish a causal relationship to drug exposure.

Immune System Disorders

Hypersensitivity reactions (including angioedema and urticaria) [see Warnings and Precautions (5.2)].

Skin and Subcutaneous Tissue Disorders

Stevens-Johnson syndrome (SJS)/toxic epidermal necrolysis (TEN) [see Warnings and Precautions (5.2)].

7 DRUG INTERACTIONS

7.1 Concomitant Use with Other Antiretroviral Medicines

VOCABRIA in combination with EDURANT (rilpivirine) is a complete regimen for the treatment of HIV-1 infection. Refer to the prescribing information for EDURANT for relevant information on rilpivirine.

Coadministration of VOCABRIA with other antiretroviral medications for PrEP is not recommended [see Drug Interactions (7.4), Clinical Pharmacology (12.3)].

Prior to initiating dosing with VOCABRIA, the prescribing information for CABENUVA (cabotegravir extended-release injectable suspension; rilpivirine extended-release injectable suspension) or APRETUDE should be consulted to ensure use of CABENUVA or APRETUDE will be appropriate for either the treatment of HIV-1 infection or HIV-1 PrEP, respectively.

7.2 Potential for Other Drugs to Affect VOCABRIA

Cabotegravir is primarily metabolized by UGT1A1 with some contribution from UGT1A9. Drugs that are strong inducers of UGT1A1 or UGT1A9 are expected to decrease cabotegravir plasma concentrations and may result in loss of efficacy; therefore, coadministration of VOCABRIA with these drugs is contraindicated [see Contraindications (4)].

Coadministration of oral cabotegravir with polyvalent cation-containing products may lead to decreased absorption of cabotegravir [see Drug Interactions (7.3)].

7.3 Established and Other Potentially Significant Drug Interactions

Information regarding potential drug interactions with cabotegravir are provided in Table 1. These recommendations are based on either drug interaction trials or predicted interactions due to the expected magnitude of the interaction and potential for loss of efficacy [see Contraindications (4), Warnings and Precautions (5.5), Clinical Pharmacology (12.3)]. Table 1 includes potentially significant interactions but is not all inclusive.

Refer to the prescribing information for EDURANT (rilpivirine) for established or potentially significant interactions that should be considered during concomitant administration of VOCABRIA and EDURANT for HIV-1 treatment.

Table 1. Drug Interactions with VOCABRIA
Concomitant Drug Class:; Drug Name | Effect on Concentration | Clinical Comment
Antacids containing polyvalent cations (e.g., aluminum or magnesium hydroxide, calcium carbonate) | ↓Cabotegravir | Administer antacid products at least 2 hours before or 4 hours after taking VOCABRIA.
Anticonvulsants:; Carbamazepine; Oxcarbazepine; Phenobarbital; Phenytoin | ↓Cabotegravir | Coadministration is contraindicated with VOCABRIA due to potential for loss of efficacy and development of resistance [see Contraindications (4)].
Antimycobacterialsa:; Rifampin; Rifapentine | ↓Cabotegravir | Coadministration is contraindicated with VOCABRIA due to potential for loss of efficacy and development of resistance [see Contraindications (4)].
Antimycobacterial:; Rifabutin | ↓Cabotegravir | Dose modification is not required for VOCABRIA. Dose modification is recommended for APRETUDE for HIV-1 PrEP. Coadministration is contraindicated with CABENUVA for HIV-1 treatment.
↓ = Decrease; PrEP = Pre-exposure prophylaxis.
a Rifabutin can be coadministered with cabotegravir; however, it is contraindicated with CABENUVA for HIV-1 treatment. Dosage modification is recommended with APRETUDE for HIV-1 PrEP.

7.4 Drugs without Clinically Significant Interactions with Cabotegravir

Based on drug interaction study results, the following drugs can be coadministered with cabotegravir without a dose adjustment: etravirine, midazolam, oral contraceptives containing levonorgestrel and ethinyl estradiol, rifabutin, and rilpivirine [see Clinical Pharmacology (12.3)].

Prior to initiating oral therapy, note that use of CABENUVA (cabotegravir extended-release injectable suspension; rilpivirine extended-release injectable suspension) with rifabutin is contraindicated for the treatment of HIV-1 infection. Dosage modification is recommended when APRETUDE is used with rifabutin for HIV-1 PrEP.

8 USE IN SPECIFIC POPULATIONS

8.1 Pregnancy

Pregnancy Exposure Registry

There is a pregnancy exposure registry that monitors pregnancy outcomes in individuals exposed to VOCABRIA during pregnancy. Healthcare providers are encouraged to register patients by calling the Antiretroviral Pregnancy Registry (APR) at 1-800-258-4263.

Risk Summary

There are insufficient human data on the use of VOCABRIA during pregnancy to adequately assess a drug-associated risk of birth defects and miscarriage. Discuss the benefit-risk of using VOCABRIA with individuals of childbearing potential or during pregnancy.

The APR has been established to monitor for birth defects following prenatal exposure to antiretrovirals. The rate of miscarriage is not reported in the APR. The background risk for major birth defects and miscarriage for the indicated population is unknown. The background rate for major birth defects in a United States (U.S.) reference population of the Metropolitan Atlanta Congenital Defects Program (MACDP) is 2.7%. The estimated background rate of miscarriage in clinically recognized pregnancies in the U.S. general population is 15% to 20%. The APR uses the MACDP as the U.S. reference population for birth defects in the general population. The MACDP evaluates mothers and infants from a limited geographic area and does not include outcomes for births that occurred at <20 weeks’ gestation.

In animal reproduction studies with oral cabotegravir, a delay in the onset of parturition and increased stillbirths and neonatal deaths were observed in a rat pre- and postnatal development study at >28 times the exposure at the recommended human dose (RHD). No evidence of adverse developmental outcomes was observed with oral cabotegravir in rats or rabbits (>28 times or similar to the exposure at the RHD, respectively) given during organogenesis (see Data).

Data

Animal Data: Cabotegravir was administered orally to pregnant rats at 0, 0.5, 5, or 1,000 mg/kg/day from 15 days before cohabitation, during cohabitation, and from Gestation Days 0 to 17. There were no effects on fetal viability when fetuses were delivered by caesarean, although a minor decrease in fetal body weight was observed at 1,000 mg/kg/day (>28 times the exposure in humans at the RHD). No drug-related fetal toxicities were observed at 5 mg/kg/day (approximately 13 times the exposure in humans at the RHD), and no drug-related fetal malformations were observed at any dose.

Cabotegravir was administered orally to pregnant rabbits at 0, 30, 500, or 2,000 mg/kg/day from Gestation Days 7 to 19. No drug-related fetal toxicities were observed at 2,000 mg/kg/day (approximately 0.7 times the exposure in humans at the RHD).

In a rat pre- and postnatal development study, cabotegravir was administered orally to pregnant rats at 0, 0.5, 5, or 1,000 mg/kg/day from Gestation Day 6 to Lactation Day 21. A delay in the onset of parturition and increases in the number of stillbirths and neonatal deaths by Lactation Day 4 were observed at 1,000 mg/kg/day (>28 times the exposure in humans at the RHD); there were no alterations to growth and development of surviving offspring. In a cross-fostering study, similar incidences of stillbirths and early postnatal deaths were observed when rat pups born to cabotegravir-treated mothers were nursed from birth by control mothers. There was no effect on neonatal survival of control pups nursed from birth by cabotegravir-treated mothers. A lower dose of 5 mg/kg/day (13 times the exposure at the RHD) was not associated with delayed parturition or neonatal mortality in rats. Studies in pregnant rats showed that cabotegravir crosses the placenta and can be detected in fetal tissue.

8.2 Lactation

Risk Summary

There are no data on the presence of cabotegravir in human milk, the effects on the breastfed infant, or the effects on milk production. Cabotegravir is present in animal milk (see Data). When a drug is present in animal milk, it is likely that the drug will be present in human milk. Potential risks of breastfeeding include: (1) HIV-1 transmission (in HIV-1–negative infants), (2) developing viral resistance (in HIV-1–positive infants), and (3) adverse reactions in a breastfed infant similar to those seen in adults.

In mothers without HIV-1, breastfeeding should only be considered if the expected benefit justifies the potential risk to the infant, including the potential risk for adverse reaction in the breastfed child, along with the risk of HIV-1 acquisition due to nonadherence and subsequent vertical transmission to the child. Breastfeeding is not recommended if acute HIV-1 infection is suspected to avoid the risk of postnatal transmission of HIV-1 infection.

Data

Animal lactation studies with cabotegravir have not been conducted. However, cabotegravir was detected in the plasma of nursing pups on Lactation Day 10 in the rat pre- and postnatal development study.

8.4 Pediatric Use

Treatment of HIV-1 Infection

The safety and effectiveness of VOCABRIA have been established in adolescents aged 12 to younger than 18 years and weighing at least 35 kg, which is supported by the following:

- Trials in adults [see Clinical Studies (14.1)]
- MOCHA (NCT03497676) trial in adolescents, in which virologically suppressed adolescents (aged 12 to younger than 18 years and weighing at least 35 kg) with HIV-1 received either cabotegravir or rilpivirine in addition to their background antiretroviral regimen (cohort 1), or cabotegravir plus rilpivirine as a complete regimen (cohort 2) [see Adverse Reactions (6.1), Clinical Pharmacology (12.3), Clinical Studies (14.3)].

The safety and efficacy of VOCABRIA in adolescents (aged 12 to younger than 18 years and weighing at least 35 kg) were similar to that in adults and there was no clinically significant change in drug exposure [see Adverse Reactions (6.1), Clinical Pharmacology (12.3)].

Please refer to the CABENUVA prescribing information for additional information.

The safety, efficacy, and pharmacokinetics of VOCABRIA have not been established in pediatric patients younger than 12 years of age or weighing <35 kg.

HIV-1 Pre-Exposure Prophylaxis

The safety and effectiveness of VOCABRIA for HIV-1 PrEP in adolescents weighing at least 35 kg who are at risk for HIV-1 acquisition is supported by data from 2 adequate and well-controlled trials of VOCABRIA for HIV-1 PrEP in adults with additional safety and pharmacokinetic data from studies in adults with HIV-1 who were administered CABENUVA and in adolescent participants with HIV-1 who were administered separate components of CABENUVA in addition to their current antiretroviral therapy [see Dosage and Administration (2.2), Adverse Reactions (6.1), Clinical Pharmacology (12.3), Clinical Studies (14.2)].

APRETUDE for HIV-1 PrEP was evaluated in 2 open-label multicenter clinical trials, HPTN 083-01 and HPTN 084-01, in adolescent individuals 12 to less than 18 years of age weighing at least 35 kg who are at risk for HIV-1 acquisition. Sixty-four adolescents were enrolled. Of these, 62 adolescent participants received one or more injections after receiving VOCABRIA. In adolescents receiving VOCABRIA and APRETUDE for HIV-1 PrEP, the safety data were comparable to the safety data reported in adults receiving APRETUDE for HIV-1 PrEP.

While using APRETUDE, HIV-1 testing should be conducted prior to initiating APRETUDE (with or without an oral lead-in with oral cabotegravir) and prior to each injection of APRETUDE. Adolescents may benefit from more frequent visits and counseling to support adherence to the dosing schedule [see Dosage and Administration (2.2), Warnings and Precautions (5.1)].

The safety, efficacy, and pharmacokinetics of VOCABRIA in pediatric participants younger than 12 years of age or weighing <35 kg have not been established.

8.5 Geriatric Use

Clinical trials of VOCABRIA did not include sufficient numbers of participants aged 65 years and older to determine whether they respond differently from younger participants. In general, caution should be exercised in administration of VOCABRIA in elderly patients, reflecting greater frequency of decreased hepatic, renal, or cardiac function and of concomitant disease or other drug therapy [see Clinical Pharmacology (12.3)].

8.6 Renal Impairment

No dosage adjustment of VOCABRIA is necessary for patients with mild to moderate (creatinine clearance equal to 30 mL/min to <90 mL/min) or severe renal impairment (creatinine clearance equal to 15 mL/min to <30 mL/min) [see Clinical Pharmacology (12.3)]. The effect of end-stage renal disease (creatinine clearance <15 mL/min) on the pharmacokinetics of cabotegravir is unknown. As cabotegravir is >99% protein bound, dialysis is not expected to alter exposures of cabotegravir.

Since VOCABRIA is taken in combination with EDURANT for the treatment of HIV-1 infection, the prescribing information for EDURANT should be consulted for additional recommendations in patients with severe impairment or end-stage renal disease.

8.7 Hepatic Impairment

No dosage adjustment of VOCABRIA is necessary for patients with mild or moderate hepatic impairment (Child-Pugh A or B). The effect of severe hepatic impairment (Child-Pugh C) on the pharmacokinetics of cabotegravir is unknown [see Clinical Pharmacology (12.3)].

10 OVERDOSAGE

There is no known specific treatment for overdose with VOCABRIA. If overdose occurs, monitor the patient and apply standard supportive treatment as required as well as observation of the clinical status of the individual. As cabotegravir is highly bound to plasma proteins, it is unlikely that it will be significantly removed by dialysis.

11 DESCRIPTION

VOCABRIA contains cabotegravir, as cabotegravir sodium, an HIV integrase strand transfer inhibitor (INSTI). The chemical name of cabotegravir sodium is sodium (3S,11aR)-N-[(2,4-difluorophenyl)methyl]-6-hydroxy-3-methyl-5,7-dioxo-2,3,5,7,11,11a-hexahydro[1,3]oxazolo[3,2-a]pyrido [1,2-d]pyrazine-8-carboxamide. The empirical formula is C19H16F2N3NaO5 and the molecular weight is 427.34 g/mol. It has the following structural formula:

Cabotegravir sodium is a white to almost white crystalline solid that is slightly soluble in water.

Each immediate-release film-coated tablet of VOCABRIA for oral administration contains 30 mg of cabotegravir (equivalent to 31.62 mg cabotegravir sodium) and the inactive ingredients: hypromellose, lactose monohydrate, magnesium stearate, microcrystalline cellulose, and sodium starch glycolate. The tablet film-coating contains hypromellose, polyethylene glycol, and titanium dioxide.

12 CLINICAL PHARMACOLOGY

12.1 Mechanism of Action

Cabotegravir is an HIV-1 antiretroviral drug [see Microbiology (12.4)].

12.2 Pharmacodynamics

Cardiac Electrophysiology

At a dose of cabotegravir 150 mg orally every 12 hours (10 times the recommended total daily oral lead-in dosage of VOCABRIA), the QT interval is not prolonged to any clinically relevant extent. Administration of 3 doses of cabotegravir 150 mg orally every 12 hours resulted in a geometric mean Cmax approximately 2.8-fold above the geometric mean steady-state Cmax associated with the recommended 30-mg dose of oral cabotegravir.

For additional QT information related to the injectable formulations of cabotegravir and rilpivirine (CABENUVA), the injectable formulation of cabotegravir (APRETUDE), and the oral formulation of rilpivirine (EDURANT), refer to the prescribing information for CABENUVA, APRETUDE, and EDURANT.

12.3 Pharmacokinetics

Absorption, Distribution, and Elimination

The pharmacokinetic properties of cabotegravir are provided in Table 2. The multiple-dose pharmacokinetic parameters are provided in Table 3.

Table 2. Pharmacokinetic Properties of Cabotegravir
Absorption
Tmax (h), median | 3
Effect of high-fat meal (relative to fasting): | 1.14
AUC(0-inf) ratioa | (1.02, 1.28)
Distribution
% Bound to human plasma proteins | >99.8
Blood-to-plasma ratio | 0.52
CSF-to-plasma concentration ratio (median [range])b | 0.003
 | (0.002 to 0.004)
Elimination
t1/2 (h), mean | 41
Metabolism
Metabolic pathways | UGT1A1
 | UGT1A9 (minor)
Excretion
Major route of elimination | Metabolism
% of dose excreted as total ^14C (unchanged drug) in urineb | 27 (0)
% of dose excreted as total ^14C (unchanged drug) in fecesb | 59 (47)
CSF = Cerebrospinal fluid.
a Geometric mean ratio (fed/fasted) in pharmacokinetic parameters and 90% confidence interval. High‑calorie/high-fat meal = 870 kcal, 53% fat.
b Dosing in mass balance studies: single-dose oral administration of [^14C] cabotegravir.

Table 3. Multiple-Dose Pharmacokinetic Parameters of Oral Cabotegravir in Adults
Parameter | Geometric Mean (5th, 95th Percentile)a
Cmax (mcg/mL) | 8.0 (5.3, 11.9)
AUC(0-tau) (mcg•h/mL)b | 145 (93.5, 224)
Ctau (mcg/mL)b | 4.6 (2.8, 7.5)
a Pharmacokinetic parameter values were based on individual post-hoc estimates from the final population pharmacokinetic model for participants receiving 30 mg of oral cabotegravir once daily in FLAIR and ATLAS trials.
b tau is dosing interval: 24 hours for oral cabotegravir.

Specific Populations

No clinically significant differences in the pharmacokinetics of cabotegravir were observed based on age, sex, race/ethnicity, body mass index, or UGT1A1 polymorphisms. The effect of hepatitis B and C virus co-infection on the pharmacokinetics of cabotegravir is unknown.

Renal Impairment: No clinically significant differences in the pharmacokinetics of cabotegravir are expected with mild, moderate, or severe renal impairment. Cabotegravir has not been studied in patients with end-stage renal disease not on dialysis. As cabotegravir is >99% protein bound, dialysis is not expected to alter exposures of cabotegravir [see Use in Specific Populations (8.6)].

Hepatic Impairment: No clinically significant differences in the pharmacokinetics of cabotegravir are expected in mild to moderate (Child-Pugh A or B) hepatic impairment. The effect of severe hepatic impairment (Child-Pugh C) on the pharmacokinetics of cabotegravir has not been studied [see Use in Specific Populations (8.7)].

Gender: Population pharmacokinetic analyses revealed no clinically relevant effect of gender on the exposure of cabotegravir. In addition, no clinically relevant differences in plasma cabotegravir concentrations were observed in PrEP studies by gender, including cisgender men and transgender women (+/-hormone use). Therefore, no dose adjustment is necessary based on gender.

Geriatric Patients: No dose adjustment is required in elderly individuals. There are limited data available on the use of cabotegravir in individuals aged 65 years and older. In general, caution should be exercised in administration of cabotegravir in elderly individuals, reflecting greater frequency of decreased hepatic, renal, or cardiac function and of concomitant disease or other drug therapy [see Use in Specific Populations (8.5)].

Pediatric Patients: Population pharmacokinetic analyses revealed no clinically relevant differences in exposure between adolescent participants (weighing ≥35 kg) and adult participants with and without HIV-1 from the cabotegravir development program; therefore, no dosage adjustment is needed for adolescents weighing ≥35 kg (Table 4).

Table 4. Pharmacokinetic Parameters following Once-Daily Oral Cabotegravir in Adolescents Aged 12 to Younger than 18 Years (≥35 kg)
Parameter | Geometric Mean (5th, 95th Percentile)a
Cmax (mcg/mL) | 10.7 (7.36, 16.6)
AUC(0-tau) (mcg•h/mL)b | 203 (136, 320)
Ctau (mcg/mL)b | 6.43 (4.15, 10.5)
a Pharmacokinetic parameter values were based on individual post-hoc estimates from population pharmacokinetic models in both adolescents with HIV-1 (n = 147) weighing 35.2 to 98.5 kg and adolescents without HIV-1 (n = 62) weighing 39.9 to 167 kg.
b tau is dosing interval: 24 hours for oral administration.

Drug Interaction Studies

Cabotegravir is not a clinically relevant inhibitor of the following enzymes and transporters: cytochrome P450 (CYP)1A2, 2A6, 2B6, 2C8, 2C9, 2C19, 2D6, and 3A4; UGT1A1, 1A3, 1A4, 1A6, 1A9, 2B4, 2B7, 2B15, and 2B17; P-glycoprotein (P-gp); breast cancer resistance protein (BCRP); bile salt export pump (BSEP); organic cation transporter (OCT)1, OCT2; organic anion transporter polypeptide (OATP)1B1, OATP1B3; multidrug and toxin extrusion transporter (MATE) 1, MATE 2-K; and multidrug resistance protein (MRP)2 or MRP4.

In vitro, cabotegravir inhibited renal OAT1 (IC50 = 0.81 microM) and OAT3 (IC50 = 0.41 microM). Based on physiologically based pharmacokinetic (PBPK) modeling, cabotegravir may increase the AUC of OAT1/3 substrates up to approximately 80%.

In vitro, cabotegravir did not induce CYP1A2, CYP2B6, or CYP3A4.

Simulations using PBPK modeling show that no clinically significant interaction is expected during coadministration of cabotegravir with drugs that inhibit UGT1A1.

In vitro, cabotegravir was not a substrate of OATP1B1, OATP1B3, OATP2B1, or OCT1.

Cabotegravir is a substrate of P-gp and BCRP in vitro; however, because of its high permeability, no alteration in cabotegravir absorption is expected with coadministration of P-gp or BCRP inhibitors.

The effects of coadministered drugs on the exposure of cabotegravir are summarized in Table 5, and the effects of cabotegravir on the exposure of coadministered drugs are summarized in Table 6.

Table 5. Effect of Coadministered Drugs on the Pharmacokinetics of Cabotegravir
Coadministered Drug(s) and Dose(s) | Dose of Cabotegravir | n | Geometric Mean Ratio (90% CI) of Cabotegravir Pharmacokinetic Parameters with/without Coadministered Drugs; No Effect = 1.00
Coadministered Drug(s) and Dose(s) | Dose of Cabotegravir | n | Cmax | AUC | Ctau or C24
Etravirine | 30 mg | 12 | 1.04 | 1.01 | 1.00
200 mg twice daily | once daily |  | (0.99, 1.09) | (0.96, 1.06) | (0.94, 1.06)
Rifabutin | 30 mg | 12 | 0.83 | 0.79 | 0.74
300 mg once daily | once daily |  | (0.76, 0.90) | (0.74, 0.83) | (0.70, 0.78)
Rifampin | 30-mg | 15 | 0.94 | 0.41 | 0.50
600 mg once daily | single dose |  | (0.87, 1.02) | (0.36, 0.46) | (0.44, 0.57)
Rilpivirine | 30 mg | 11 | 1.05 | 1.12 | 1.14
25 mg once daily | once daily |  | (0.96, 1.15) | (1.05, 1.19) | (1.04, 1.24)
n = Maximum number of participants with data, CI = Confidence Interval.

Table 6. Effect of Cabotegravir on the Pharmacokinetics of Coadministered Drugs
Coadministered Drug(s) and Dose(s) | Dose of Cabotegravir | n | Geometric Mean Ratio (90% CI) of Pharmacokinetic Parameters of Coadministered Drug with/without Cabotegravir; No Effect = 1.00
Coadministered Drug(s) and Dose(s) | Dose of Cabotegravir | n | Cmax | AUC | Ctau or C24
Ethinyl estradiol | 30 mg | 19 | 0.92 | 1.02 | 1.00
0.03 mg once daily | once daily |  | (0.83, 1.03) | (0.97, 1.08) | (0.92, 1.10)
Levonorgestrel | 30 mg | 19 | 1.05 | 1.12 | 1.07
0.15 mg once daily | once daily |  | (0.96, 1.15) | (1.07, 1.18) | (1.01, 1.15)
Midazolam | 30 mg | 12 | 1.09 | 1.10 | NA
3 mg | once daily |  | (0.94, 1.26) | (0.95, 1.26)
Rilpivirine | 30 mg | 11 | 0.96 | 0.99 | 0.92
25 mg once daily | once daily |  | (0.85, 1.09) | (0.89, 1.09) | (0.79, 1.07)
n = Maximum number of participants with data, CI = Confidence Interval, NA = Not available.

12.4 Microbiology

Mechanism of Action

Cabotegravir inhibits HIV integrase by binding to the integrase active site and blocking the strand transfer step of retroviral deoxyribonucleic acid (DNA) integration that is essential for the HIV replication cycle. The mean 50% inhibitory concentration (IC50) value of cabotegravir in a strand transfer assay using purified recombinant HIV-1 integrase was 3.0 nM.

Antiviral Activity in Cell Culture

Cabotegravir exhibited antiviral activity against laboratory strains of HIV-1 (subtype B, n = 4) with mean 50 percent effective concentration (EC50) values of 0.22 to 1.7 nM in peripheral blood mononuclear cells (PBMCs) and 293 cells. Cabotegravir demonstrated antiviral activity in PBMCs against a panel of 24 HIV-1 clinical isolates (3 in each of group M subtypes A, B, C, D, E, F, and G and 3 in group O) with a median EC50 value of 0.19 nM (range: 0.02 to 1.06 nM, n = 24). The median EC50 value against subtype B clinical isolates was 0.05 nM (range: 0.02 to 0.50 nM, n = 3). Against clinical HIV-2 isolates, the median EC50 value was 0.12 nM (range: 0.10 to 0.14 nM, n = 3).

In cell culture, cabotegravir was not antagonistic in combination with the non-nucleoside reverse transcriptase inhibitor (NNRTI) rilpivirine, or the nucleoside reverse transcriptase inhibitors (NRTIs) emtricitabine (FTC), lamivudine (3TC), or tenofovir disoproxil fumarate (TDF).

Resistance

Cell Culture: Cabotegravir-resistant viruses were selected during passage of HIV-1 strain IIIB in MT-2 cells in the presence of cabotegravir. Amino acid substitutions in integrase that emerged and conferred decreased susceptibility to cabotegravir included Q146L (fold change: 1.3 to 4.6), S153Y (fold change: 2.8 to 8.4), and I162M (fold change: 2.8). The integrase substitution T124A also emerged alone (fold change: 1.1 to 7.4 in cabotegravir susceptibility), in combination with S153Y (fold change: 3.6 to 6.6 in cabotegravir susceptibility) or I162M (2.8-fold change in cabotegravir susceptibility). Cell culture passage of virus harboring integrase substitutions Q148H, Q148K, or Q148R selected for additional substitutions (C56S, V72I, L74M, V75A, T122N, E138K, G140S, G149A, and M154I), with substituted viruses having reduced susceptibility to cabotegravir of 2.0- to 410-fold change. The combinations of E138K+Q148K and V72I+E138K+Q148K conferred the greatest reductions of 53- to 260-fold change and 410-fold change, respectively.

Clinical Trials: Treatment of HIV-1 Infection: In the pooled Phase 3 FLAIR (Week 124) and ATLAS (Week 96) analysis, there were 8 confirmed virologic failures (2 consecutive HIV-1 RNA ≥200 copies/mL) on cabotegravir plus rilpivirine (8/591, 1.4%) and 8 confirmed virologic failures on current antiretroviral regimen (8/591, 1.4%). Of the 8 confirmed virologic failures in the cabotegravir plus rilpivirine arm, 7 (88%) had treatment-emergent NNRTI resistance-associated substitutions K101E, V106V/A, V108I, E138A, E138G, E138K, H221H/L, or M230L in reverse transcriptase, and 6 of them showed reduced phenotypic susceptibility to rilpivirine (range: 2- to 27-fold). One additional participant in the ATLAS Extension Switch on cabotegravir plus rilpivirine had emergent NNRTI resistance substitution E138A at Week 80 with HIV-1 RNA >50 copies/mL and <200 copies/mL.

Additionally, 5 of the 8 (63%) cabotegravir plus rilpivirine confirmed virologic failures had treatment-emergent INSTI resistance-associated substitutions and reduced phenotypic susceptibility to cabotegravir: Q148R (n = 2; 5- and 9-fold decreased susceptibility to cabotegravir), G140R (n = 1; 7-fold decreased susceptibility to cabotegravir), N155H (n = 1; 3-fold decreased susceptibility to cabotegravir), or N155H+R263K (n = 1; 9-fold decreased susceptibility to cabotegravir).

There was another confirmed virologic failure participant at Week 112 in FLAIR who had switched to cabotegravir plus rilpivirine direct to injection at Week 100; there were no INSTI resistance-associated substitutions detected at failure.

In comparison, in the current antiretroviral regimen arm with 8 confirmed virologic failures, 2 of 7 (29%) who had post‑baseline resistance data had treatment-emergent resistance substitutions and phenotypic resistance to their antiretroviral drugs; both had treatment-emergent NRTI substitutions, M184V or I, which conferred resistance to emtricitabine or lamivudine in their regimen, and one of them also had the treatment-emergent NNRTI resistance substitution G190S, which conferred resistance to efavirenz in their regimen.

In the ATLAS-2M trial, there were 11 confirmed virologic failures (2 consecutive HIV-1 RNA ≥200 copies/mL) through Week 48: 9 participants (1.7%) in the every-2-month treatment arm and 2 participants (0.4%) in the monthly treatment arm. Of note, 8 of the 11 (73%) participants met confirmed virologic failure criteria at or before the Week 24 injection visit.

Four of the 9 confirmed virologic failure participants in the every-2-month arm transitioned from the oral current antiretroviral regimen arm of ATLAS into this trial.

In the every-2-month treatment arm, 8 of 9 (89%) confirmed virologic failure participants had NNRTI resistance-associated substitutions (E138E/K+V179V/I, K101E+E138A, A98G+K103N, E138K, V179I+Y188L+P225H, Y188L, K103N+E138A, or K101E) at virologic failure. Decreases in rilpivirine susceptibility for these 8 participant isolates ranged from 2- to 30-fold. Six of the 8 participants with NNRTI resistance-associated substitutions also had INSTI resistance-associated substitutions (L74I+Q148Q/R+N155N/H (n = 2), L74I+T97A+N155H, L74I+N155H, N155H, or L74I+Q148R) at failure with cabotegravir fold changes ranging from 1- to 9-fold. The INSTI polymorphism L74I was detected at baseline in 5 of the virologic failure participants by a HIV-1 proviral DNA assay.

In the monthly treatment arm, both of the confirmed virologic failure participants had NNRTI resistance-associated substitutions (K101E+M230L or Y188F+G190Q) at virologic failure with decreased susceptibility to rilpivirine of 17- and >119.2-fold, respectively. Both participants also had INSTI resistance-associated substitutions (N155N/H or Q148R+E138E/K) at failure with decreased susceptibility to cabotegravir of 2- and 5-fold, respectively. Neither participant had the L74I integrase polymorphism at baseline.

Genotypic Baseline Factors Associated with Virologic Failure

An increased risk of cabotegravir plus rilpivirine confirmed virologic failure is associated with baseline virological factors: HIV-1 subtype A1, the presence of baseline integrase L74I polymorphism, and archived NNRTI resistance-associated substitutions.

Association of Subtype A1 and Baseline L74I Polymorphism in Integrase with Cabotegravir plus Rilpivirine Virologic Failure

Eight of the 18 (44%) cabotegravir plus rilpivirine confirmed virologic failures in FLAIR, ATLAS, and ATLAS-2M had HIV-1 subtype A1 with 7 of the 8 subtype A1 failures having the integrase polymorphism L74I detected at baseline and failure timepoints (Table 7). There was no detectable phenotypic resistance to cabotegravir conferred by the presence of L74I at baseline.

Subtype A1 is uncommon in the U.S.

The presence of the integrase polymorphism L74I in subtype B commonly seen in the U.S. was not associated with virologic failure. In contrast to FLAIR and ATLAS, where all virologic failures were subtype A, A1, or AG, subtypes of the cabotegravir plus rilpivirine virologic failures in ATLAS-2M included A (n = 1), A1 (n = 3), B (n = 4), C (n = 2), and complex/A1 (n = 1).

Association of Archived Baseline NNRTI Substitutions with Cabotegravir plus Rilpivirine Virologic Failure

The presence of archived NNRTI resistance-associated substitutions at baseline detected using an exploratory HIV-1 proviral DNA assay was associated with a higher virologic failure rate in the every-2-month arm of ATLAS-2M and in the cabotegravir plus rilpivirine arm (monthly) of ATLAS compared to without archived NNRTI resistance-associated substitutions (Table 7). However, in clinical practice, it is unlikely baseline resistance testing will be performed on virologically suppressed patients (HIV-1 RNA <50 copies/mL). Thus, in patients with an incomplete or uncertain NNRTI treatment history, consideration should be given before starting cabotegravir plus rilpivirine treatment.

Table 7. Rate of Confirmed Virologic Failure in FLAIR, ATLAS, and ATLAS-2M: Baselinea Analysis (Subtype Al, Presence of lntegrase Polymorphism L74I, and Presence of Archived NNRTI Resistance-Associated Substitutions)
 | FLAIR CAB+RPV N = 283 | FLAIR CAR N = 283 | ATLAS CAB+RPV N = 308 | ATLAS CAR N = 308 | ATLAS‑2M Q4W N = 523 | ATLAS‑2M Q8W N = 522
Total confirmed virologic failures | 5 | 4 | 3 | 4 | 2 | 9
Subtype A1b | 4/8 (50%) | 1/4 (25%) | 1/17 (6%) | 0/21 (0%) | 0/30 (0%) | 4/31 (13%)
+L74Ic | 4/5 (80%) | 1/3 (33%) | 1/16 (6%) | 0/19 (0%) | 2/28 (0%) | 3/26 (12%)
-L74I | 0/3 (0%) | 0/1 (0%) | 0/1 (0%) | 0/2 (0%) | 0/2 (0%) | 1/5 (20%)
Other subtypes | 2/268 (0.7%) | 3/272 (1%) | 2/240 (0.8%) | 4/252 (1.6%) | 2/409 (0.5%) | 5/415 (1.2%)
+L74Ic | 0/49 (0%) | 1/43 (2.3%) | 1/29 (3%) | 1/39 (2.6%) | 0/42 (0%) | 2/48 (4%)
-L74I | 0/219 (2.5%) | 2/229 (0.9%) | 1/211 (0.5%) | 3/213 (1.4%) | 2/367 (0.5%) | 3/367 (0.8%)
Missing data | 7 | 7 | 51 | 35 | 84 | 76
With NNRTI RASd | NA | NA | 3/78 (4%) | 2/83 (2%) | 1/128 (0.8%) | 7/117 (6%)
Without NNRTI RAS | NA | NA | 0/179 (0%) | 2/190 (1%) | 1/310 (0.3%) | 2/327 (0.6%)
Missing data | NA | NA | 51 | 35 | 84 | 76
NNRTI = Non-Nucleoside Reverse Transcriptase Inhibitor, CAB+RPV = Cabotegravir + Rilpivirine, CAR = Current Antiretroviral Regimen, RAS = resistance-associated substitutions, NA = Not available.
a Baseline and/or Screening result used.
b Per Standard Monogram Nomenclature Reports. Based on June 2020 Los Alamos National Library panel, the majority of HIV-1 subtype A1 was reclassified as HIV-1 subtype A6.
c L74I and L74L/I mixture.
d Baseline/Screening NNRTI substitutions at L100, K101, K103, V106, V108, E138, V179, Y181, Y188, G190, H221, P225, M230.

HIV-1 PrEP: There were 12 incident infections and 4 prevalent infections among participants receiving cabotegravir injection for HIV-1 PrEP in HPTN 083. Genotypic data were generated for viruses from 13 of these 16 participants (4 participants with prevalent infections and 9 participants with incident infections) and phenotypic data were generated for 3 of these viruses. INSTI resistance-associated substitutions were detected in 5 viruses from participants who achieved target plasma concentrations of cabotegravir (≥0.65 mcg/mL [1.6 microM]) and included R263K (2-fold less susceptible to cabotegravir), E138A+Q148R (6-fold less susceptible to cabotegravir), E138K+Q148K, G140A+Q148R (13-fold less susceptible to cabotegravir), and L74I+E138E/K+G140G/S+Q148R+E157Q.

There were 3 incident infections and 1 prevalent infection among participants receiving cabotegravir injection for HIV-1 PrEP in HPTN 084. All 3 incident infections occurred during periods with cabotegravir exposures below the target concentration. No variants expressing INSTI resistance-associated substitutions were detected.

Cross-Resistance

Cross-resistance has been observed among INSTIs. Cabotegravir had reduced susceptibility (>5-fold change) to recombinant HIV-1 strain NL432 viruses harboring the following integrase amino acid substitutions: G118R, Q148K, Q148R, T66K+L74M, E92Q+N155H, E138A+Q148R, E138K+Q148K/R, G140C+Q148R, G140S+Q148H/K/R, Y143H+N155H, and Q148R+N155H (range: 5.1- to 81-fold). The substitutions E138K+Q148K and Q148R+N155H conferred the greatest reductions in susceptibility of 81- and 61-fold, respectively.

Cabotegravir was active against viruses harboring the NNRTI substitutions K103N or Y188L, or the NRTI substitutions M184V, D67N/K70R/T215Y, or V75I/F77L/F116Y/Q151M.

Virologic failure isolates from cabotegravir plus rilpivirine treatment in FLAIR, ATLAS, and ATLAS-2M exhibited cross-resistance to INSTIs and NNRTIs. All confirmed virologic isolates with genotypic evidence of cabotegravir resistance had cross-resistance to elvitegravir and raltegravir but retained phenotypic susceptibility to dolutegravir and when tested bictegravir.

Viruses harboring E138A+Q148R or G140A+Q148R with reduced susceptibility to cabotegravir were isolated from participants using cabotegravir injection for HIV-1 PrEP in HPTN 083. These viruses remained susceptible to bictegravir and dolutegravir but had cross-resistance to elvitegravir and raltegravir.

13 NONCLINICAL TOXICOLOGY

13.1 Carcinogenesis, Mutagenesis, Impairment of Fertility

Carcinogenesis

Two-year carcinogenicity studies in mice and rats were conducted with cabotegravir. In mice, no drug-related increases in tumor incidence were observed at cabotegravir exposures (AUC) up to approximately 8 times (males) and 7 times (females) higher than those in humans at the RHD. In rats, no drug-related increases in tumor incidence were observed at cabotegravir exposures up to approximately 26 times higher than those in humans at the RHD.

Mutagenesis

Cabotegravir was not genotoxic in the bacterial reverse mutation assay, mouse lymphoma assay, or in the in vivo rodent micronucleus assay.

Impairment of Fertility

In rats, no effects on fertility were observed at cabotegravir exposures (AUC) >20 times (male) and 28 times (female) the exposure in humans at the RHD.

14 CLINICAL STUDIES

14.1 Clinical Trials in Adults for Treatment of HIV-1 Infection

The use of VOCABRIA in combination with EDURANT as an oral lead-in and in patients who miss planned injections with CABENUVA was evaluated in 3 Phase 3 randomized, multicenter, active-controlled, parallel-arm, open-label, non-inferiority trials (Trial 201584: FLAIR [NCT02938520], Trial 201585: ATLAS [NCT02951052], and Trial 207966: ATLAS‑2M [NCT03299049]) in participants who were virologically suppressed (HIV-1 RNA <50 copies/mL). Please refer to the CABENUVA prescribing information for additional information.

In the FLAIR study during the Extension Phase (Week 100 to Week 124), the efficacy of CABENUVA was evaluated in participants who switched (at Week 100) from their current antiretroviral regimen to CABENUVA, with and without an oral lead-in phase. A total of 121 participants chose to start the treatment with oral lead-in and 111 participants chose direct to injection. Participants were not randomized during the Extension Phase. At Week 124, the proportion of participants with HIV-1 RNA ≥50 copies/mL was 0.8% and 0.9% for the oral lead-in and direct to injection groups, respectively. The rates of virologic suppression (HIV-1 RNA <50 copies/mL) were similar in both the oral lead-in (93%) and direct to injection (99%) groups.

14.2 Clinical Trials in Adults for HIV-1 Pre-Exposure Prophylaxis

The use of VOCABRIA as an oral lead-in and in participants who miss planned injections with APRETUDE to reduce the risk of acquiring HIV-1 infection were evaluated in 2 randomized, double-blind, controlled, multinational trials, Trial 201738 (HPTN 083 [NCT02720094]) in men and transgender women without HIV-1 who have sex with men and have evidence of high-risk behavior for HIV-1 infection and Trial 201739 (HPTN 084 [NCT03164564]) in cisgender women without HIV-1 at risk of acquiring HIV-1. Please refer to the APRETUDE prescribing information for additional information.

14.3 Clinical Trial in Adolescents for Treatment of HIV-1 Infection

Trial 208580 (MOCHA, [NCT03497676])

The safety, tolerability, and pharmacokinetics of oral and injectable cabotegravir and oral and injectable rilpivirine were assessed in an ongoing Phase 1/2 multicenter, open-label, non‑comparative study, MOCHA (IMPAACT 2017), in virologically suppressed adolescents with HIV-1 aged 12 to younger than 18 years and weighing ≥35 kg [see Adverse Reactions (6.1), Clinical Pharmacology (12.3)].

The primary objective at Week 24 was to confirm the safety of injectable cabotegravir plus injectable rilpivirine in virologically suppressed adolescents with HIV-1. Antiviral activity was assessed as a secondary objective. A total of 144 adolescent participants with HIV-1 received oral cabotegravir in combination with oral rilpivirine as an oral lead-in. Please refer to the CABENUVA prescribing information for additional information.

16 HOW SUPPLIED/STORAGE AND HANDLING

Each VOCABRIA tablet contains 30 mg of cabotegravir and is a white, oval, film-coated, biconvex tablet debossed with “SV CTV” on one side.

Bottle of 30 tablets with child-resistant closure NDC 49702-248-13.

Store below 30°C (86°F).

17 PATIENT COUNSELING INFORMATION

Advise the patient to read the FDA-approved patient labeling (Patient Information).

Important Information for Individuals without HIV-1 Taking VOCABRIA for HIV-1 PrEP

Advise individuals without HIV-1 about the following [see Warnings and Precautions (5.1)]:

- VOCABRIA should be used for PrEP as part of an overall HIV-1 infection prevention strategy, including adherence to the dosing schedule and safer sex practices, including condoms, to reduce the risk of STIs.
- VOCABRIA is not always effective in preventing HIV-1 acquisition [see Clinical Studies (14.2)]. The time from initiation of VOCABRIA for HIV-1 PrEP to maximal protection against HIV-1 infection is unknown.
- Counsel individuals on the use of other prevention measures (e.g., knowledge of partner HIV-1 status, testing for STIs condom use). Inform individuals about and support their efforts in reducing sexual risk behavior.
- VOCABRIA should be used to reduce the risk of acquiring HIV-1 only in individuals confirmed to be HIV-1 negative [see Contraindications (4), Warnings and Precautions (5.1)]. HIV-1 resistance substitutions may emerge in individuals with undiagnosed HIV-1 infection who are taking only VOCABRIA, because VOCABRIA alone does not constitute a complete regimen for HIV-1 treatment; therefore, care should be taken to minimize the risk of initiating or continuing VOCABRIA before confirming the individual is HIV-1 negative.
- If recent (<1 month) exposures to HIV-1 are suspected or clinical symptoms consistent with acute HIV-1 infection are present, use a test approved or cleared by the FDA as an aid in the diagnosis of acute or primary HIV-1 infection.
- If an HIV-1 test indicates possible HIV-1 infection, or if symptoms consistent with acute HIV-1 infection develop following an exposure event, additional HIV testing to determine HIV status is needed. If an individual has confirmed HIV-1 infection, then the individual must be transitioned to a complete HIV-1 treatment regimen.

Hypersensitivity Reactions

Advise patients to immediately contact their healthcare provider if they develop a rash. Instruct patients to immediately stop taking VOCABRIA and seek medical attention if they develop a rash associated with any of the following symptoms as it may be a sign of a more serious reaction such as Stevens-Johnson syndrome (SJS)/toxic epidermal necrolysis (TEN): fever; generally ill feeling; extreme tiredness; muscle or joint aches; blisters; oral blisters or lesions; eye inflammation; facial swelling; swelling of the eyes, lips, tongue, or mouth; difficulty breathing; and/or signs and symptoms of liver problems (e.g., yellowing of the skin or whites of the eyes; dark or tea-colored urine; pale-colored stools or bowel movements; nausea; vomiting; loss of appetite; or pain, aching, or sensitivity on the right side below the ribs). Advise patients that if hypersensitivity occurs, they will be closely monitored, laboratory tests will be ordered, and appropriate therapy will be initiated [see Warnings and Precautions (5.2)].

Hepatotoxicity

Inform patients that hepatotoxicity has been reported with cabotegravir [see Warnings and Precautions (5.3), Adverse Reactions (6.1)]. Inform patients that monitoring for liver transaminases is recommended when VOCABRIA is used for HIV-1 treatment. Inform individuals that clinical and laboratory monitoring should be considered and APRETUDE should be discontinued if hepatoxicity is confirmed when VOCABRIA is used for HIV-1 PrEP [see Warnings and Precautions (5.3)].

Depressive Disorders

Inform patients that depressive disorders (including depressed mood, depression, mood altered, mood swings, suicidal ideation/suicide attempt) have been reported with VOCABRIA for treatment of HIV-1. Inform patients that depressive disorders (including depression, depressed mood, persistent depressive disorder, suicidal ideation/suicide attempt) have been reported with VOCABRIA for HIV-1 PrEP. Promptly evaluate patients with severe depressive symptoms to assess whether the symptoms are related to VOCABRIA and to determine whether the risks of continued therapy outweigh the benefits [see Warnings and Precautions (5.4), Adverse Reactions (6.1)].

Drug Interactions

Inform patients that VOCABRIA may interact with other drugs and may reduce exposure of VOCABRIA; therefore, advise patients to report to their healthcare provider the use of any other prescription or nonprescription medication or herbal products [see Contraindications (4), Warnings and Precautions (5.5), Drug Interactions (7.2, 7.3)].

Dosage and Administration

Inform patients that it is important to take VOCABRIA once daily on a regular dosing schedule with a meal at the same time as EDURANT for HIV-1 treatment and to avoid missing doses, as this can result in development of resistance. Instruct patients that if they miss a dose of VOCABRIA to take it as soon as they remember [see Dosage and Administration (2.1), Clinical Pharmacology (12.3)].

Pregnancy Registry

Inform patients that there is an antiretroviral pregnancy registry to monitor fetal outcomes in those exposed to VOCABRIA during pregnancy [see Use in Specific Populations (8.1)].

Lactation

Inform individuals with HIV-1 infection that the potential risks of breastfeeding include: (1) HIV-1 transmission (in HIV-1–negative infants), (2) developing viral resistance (in HIV‑1‑positive infants), and (3) adverse reactions in a breastfed infant similar to those seen in adults.

In mothers without HIV-1, the benefits and risks of VOCABRIA while breastfeeding should be evaluated, including the risk of HIV-1 acquisition due to medication nonadherence and subsequent mother to child transmission. Instruct mothers not to breastfeed if acute HIV‑1 infection is suspected because of the risk of passing the HIV-1 virus to the baby [see Use in Specific Populations (8.2)].

APRETUDE, CABENUVA, and VOCABRIA are trademarks owned by or licensed to the ViiV Healthcare group of companies.

The other brands listed are trademarks owned by or licensed to their respective owners and are not trademarks owned by or licensed to the ViiV Healthcare group of companies. The makers of these brands are not affiliated with and do not endorse the ViiV Healthcare group of companies or its products.

Manufactured for:

ViiV Healthcare
Durham, NC 27701

©2025 ViiV Healthcare group of companies or its licensor.

VCB:10PI

PATIENT INFORMATION

VOCABRIA [voe-KAB-ree-ah]

(cabotegravir)

tablets, for oral use

This Patient Information provides information about two different ways that VOCABRIA may be used. See the section “What is VOCABRIA?” for detailed information about how VOCABRIA may be used.

What is the most important information I should know about VOCABRIA?

Important information for people who take VOCABRIA to help reduce their risk of getting human immunodeficiency virus-1 (HIV-1) infection, also called pre-exposure prophylaxis or “PrEP”:

Before taking VOCABRIA to reduce your risk of getting HIV-1:

- You must be HIV-1 negative to start VOCABRIA. You must get tested to make sure that you do not already have HIV-1 infection.
- Do not take VOCABRIA for HIV-1 PrEP unless you are confirmed to be HIV-1 negative.
- Some HIV-1 tests can miss HIV-1 infection in a person who has recently become infected. If you have flu-like symptoms, you could have recently become infected with HIV-1. Tell your healthcare provider if you had a flu‑like illness within the last month before starting VOCABRIA or at any time while taking VOCABRIA. Symptoms of new HIV-1 infection include:

- tiredness
- joint or muscle aches
- sore throat
- rash
- enlarged lymph nodes in the neck or groin

- fever
- headache
- vomiting or diarrhea
- night sweats

While you are taking VOCABRIA for HIV-1 PrEP:

- VOCABRIA does not prevent other sexually transmitted infections. Practice safer sex by using a latex or polyurethane condom to reduce the risk of getting sexually transmitted infections.
- You must stay HIV-1 negative to keep taking VOCABRIA for HIV-1 PrEP.
  - Know your HIV-1 status and the HIV-1 status of your partners.
  - Ask your partners with HIV-1 if they are taking anti-HIV-1 medicines and have an undetectable viral load. An undetectable viral load is when the amount of virus in the blood is too low to be measured in a lab test. To maintain an undetectable viral load, your partners must keep taking HIV-1 medicine as prescribed. Your risk of getting HIV-1 is lower if your partners with HIV-1 are taking effective treatment.
  - Get tested for HIV-1 when your healthcare provider tells you.
  - Get tested for other sexually transmitted infections such as syphilis, chlamydia, and gonorrhea. These infections make it easier for HIV-1 to infect you.
  - If you think you were exposed to HIV-1, tell your healthcare provider right away. They may want to do more tests to be sure you are still HIV-1 negative.
  - Get information and support to help reduce sexual risk behaviors.
  - Do not miss any doses of VOCABRIA. Missing doses increases your risk of getting HIV-1 infection.
  - If you do become HIV-1 positive, you will need to take other medicines to treat HIV-1. VOCABRIA by itself is not a complete treatment for HIV-1.

If you have HIV-1 and take only VOCABRIA, over time your HIV-1 may become harder to treat.

What is VOCABRIA?

VOCABRIA is a prescription medicine that may be used in two different ways when a person’s healthcare provider determines that they meet certain requirements. VOCABRIA is used:

- to treat HIV-1 infection
  - in combination with another HIV-1 medicine called EDURANT (rilpivirine) for short-term treatment of HIV-1 infection in people 12 years of age and older who weigh at least 77 pounds (35 kg) to replace their current HIV-1 medicines to assess the tolerability of cabotegravir before receiving the long-acting medicine called CABENUVA (cabotegravir extended-release injectable suspension; rilpivirine extended-release injectable suspension).
  - as oral therapy for people who will miss planned injection dosing with CABENUVA.
- for HIV-1 PrEP to reduce the risk of getting HIV-1 infection
  - for short-term PrEP in adults and adolescents who weigh at least 77 pounds (at least 35 kg) to assess the tolerability of cabotegravir before receiving the long-acting medicine called APRETUDE (cabotegravir extended-release injectable suspension).
  - as oral dosing for people who will miss planned injection dosing with APRETUDE.

HIV-1 is the virus that causes Acquired Immune Deficiency Syndrome (AIDS).

If you are taking VOCABRIA to treat HIV-1 infection, you should also read the Patient Information for EDURANT.

It is not known if VOCABRIA for treatment of HIV-1 infection is safe and effective in children younger than 12 years of age or weighing less than 77 pounds (35 kg).

It is not known if VOCABRIA is safe and effective in reducing the risk of HIV-1 infection in children younger than 12 years of age or weighing less than 77 pounds (less than 35 kg).

Do not take VOCABRIA if you:

- have ever had an allergic reaction to cabotegravir.
- are taking any of the following medicines:

- carbamazepine
- oxcarbazepine
- phenobarbital

- phenytoin
- rifampin
- rifapentine

For people taking VOCABRIA for treatment of HIV-1 infection:

Do not take VOCABRIA for HIV-1 infection if you are taking rifabutin.

For people taking VOCABRIA for HIV-1 PrEP:

Do not take VOCABRIA for HIV-1 PrEP if you:

- already have HIV-1 infection. If you are HIV-1 positive, you will need to take other medicines to treat HIV-1. VOCABRIA by itself is not a complete treatment for HIV-1.
- do not know your HIV-1 infection status. You may already be HIV-1 positive. You need to take other medicines to treat HIV-1. VOCABRIA can only help reduce your risk of getting HIV-1 infection before you are infected.
- are allergic to cabotegravir.
- are taking any of the medicines listed above. See “Do not take VOCABRIA for HIV-1 infection if you:”

Before taking VOCABRIA, tell your healthcare provider about all your medical conditions, including if you:

- have ever had a skin rash or an allergic reaction to medicines that contain cabotegravir.
- have or have had liver problems, including hepatitis B or C infection.
- have ever had mental health problems.
- are pregnant or plan to become pregnant. It is not known if VOCABRIA will harm your unborn baby. Tell your healthcare provider if you become pregnant during treatment with VOCABRIA.
  Pregnancy Registry. There is a pregnancy registry for those who take VOCABRIA during pregnancy. The purpose of this registry is to collect information about the health of you and your baby. Talk to your healthcare provider about how you can take part in this registry.
- are breastfeeding or plan to breastfeed. VOCABRIA may pass into your breast milk.
  - If you take VOCABRIA to treat HIV-1 infection, talk to your healthcare provider about the following risks to your baby from breastfeeding during treatment with VOCABRIA:
    - the HIV-1 virus may pass to your baby if your baby does not have HIV-1 infection.
    - the HIV-1 virus may become harder to treat if your baby has HIV-1 infection.
    - your baby may get side effects from VOCABRIA.
  - If you take VOCABRIA for HIV-1 PrEP, talk with your healthcare provider about the best way to feed your baby while receiving VOCABRIA.

Tell your healthcare provider about all the medicines you take, including prescription and over-the-counter medicines, vitamins, and herbal supplements.

Some medicines may interact with VOCABRIA. Keep a list of your medicines and show it to your healthcare provider and pharmacist when you get a new medicine.

You can ask your healthcare provider or pharmacist for a list of medicines that interact with VOCABRIA.

Do not start taking a new medicine without telling your healthcare provider. Your healthcare provider can tell you if it is safe to take VOCABRIA with other medicines.

How should I take VOCABRIA?

- For treatment of HIV-1 infection:
  - Take 1 VOCABRIA tablet and 1 EDURANT tablet 1 time a day for 1 month (at least 28 days) exactly as your healthcare provider tells you.
  - Your healthcare provider may have you take VOCABRIA tablets in combination with EDURANT tablets for 1 month (at least 28 days) before you receive CABENUVA for the first time. This will allow your healthcare provider to assess how well you will tolerate these medicines.
  - Your final dose of VOCABRIA and EDURANT should be taken on the same day you receive your first injections of CABENUVA.
  - If you miss or plan to miss a scheduled monthly or every-2-month injections of CABENUVA by more than 7 days, call your healthcare provider right away to discuss your options.
  - If you take VOCABRIA at the same time as EDURANT, you should take it with a meal.
  - Do not run out of VOCABRIA. The virus in your blood may increase and the virus may become harder to treat when using VOCABRIA to treat HIV-1 infection.
- For HIV-1 PrEP:
  - Take 1 VOCABRIA tablet 1 time a day for 1 month (at least 28 days) exactly as your healthcare provider tells you.
  - Your healthcare provider may have you take VOCABRIA tablets for 1 month (at least 28 days) before you receive APRETUDE for the first time. This will allow your healthcare provider to assess how well you will tolerate APRETUDE.
  - You should receive your first injection of APRETUDE on the day of your last dose of VOCABRIA or within 3 days.
  - If you miss or plan to miss a scheduled every-2-month injection of APRETUDE by more than 7 days, call your healthcare provider right away to discuss your options.
- VOCABRIA may be taken with or without food.
- If you take antacid products that contain aluminum or magnesium hydroxide or calcium carbonate, they should be taken at least 2 hours before or 4 hours after you take VOCABRIA.
- Stay under the care of a healthcare provider while taking VOCABRIA.
- Do not change your dose or stop taking VOCABRIA without talking to your healthcare provider.
- Do not miss a dose of VOCABRIA. If you miss a dose of VOCABRIA, take it as soon as you remember.
- If you take too much VOCABRIA, call your healthcare provider or go to the nearest hospital emergency room right away.

What are the possible side effects of VOCABRIA?

VOCABRIA may cause serious side effects including:

- Allergic reactions. Call your healthcare provider right away if you develop a rash with VOCABRIA.
  Stop taking VOCABRIA and get medical help right away if you develop a rash with any of the following signs or symptoms:

- fever
- generally ill feeling
- tiredness
- muscle or joint aches
- trouble breathing

- blisters or sores in mouth
- blisters
- redness or swelling of the eyes
- swelling of the mouth, face, lips, or tongue

- Liver problems. Liver problems have happened in people with or without history of liver problems or other risk factors. Your healthcare provider may do blood tests to check your liver function. People with a history of liver problems or people who have certain liver function test changes may have an increased risk of developing new or worsening changes in certain liver tests during treatment with VOCABRIA.
  Call your healthcare provider right away if you develop any of the following signs or symptoms of liver problems:

- your skin or the white part of your eyes turns yellow (jaundice)
- dark or “tea-colored” urine
- light-colored stools (bowel movements)
- nausea or vomiting

- loss of appetite
- pain, aching, or tenderness on the right side of your stomach area
- itching

- Depression or mood changes. Call your healthcare provider or get medical help right away if you develop any of the following symptoms:
  - feeling sad or hopeless
  - feeling anxious or restless
  - have thoughts of hurting yourself (suicide) or have tried to hurt yourself

The most common side effects of VOCABRIA for HIV-1 treatment include:

- fatigue
- headache
- diarrhea
- nausea
- dizziness
- abnormal dreams

- anxiety
- sleep disorders
- stomach pain
- stomach bloating
- weakness

The most common side effects of VOCABRIA for HIV-1 PrEP include:

- headache
- diarrhea
- nausea
- dizziness
- upper respiratory tract infection

- tiredness
- drowsiness
- abnormal dreams
- stomach pain

These are not all the possible side effects of VOCABRIA.

Call your doctor for medical advice about side effects. You may report side effects to FDA at 1‑800‑FDA‑1088.

How should I store VOCABRIA?

Store VOCABRIA below 86°F (30°C).

Keep VOCABRIA and all medicines out of the reach of children.

General information about the safe and effective use of VOCABRIA.

Medicines are sometimes prescribed for purposes other than those listed in a Patient Information leaflet. Do not use VOCABRIA for a condition for which it was not prescribed. Do not give VOCABRIA to other people, even if they have the same symptoms that you have. It may harm them. You can ask your pharmacist or healthcare provider for information about VOCABRIA that is written for health professionals.

What are the ingredients in VOCABRIA?

Active ingredient: cabotegravir

Inactive ingredients: hypromellose, lactose monohydrate, magnesium stearate, microcrystalline cellulose, and sodium starch glycolate.

The tablet film-coating contains: hypromellose, polyethylene glycol and titanium dioxide.

Manufactured for:

ViiV Healthcare

Durham, NC 27701

APRETUDE, CABENUVA, and VOCABRIA are trademarks owned by or licensed to the ViiV Healthcare group of companies.

The other brand listed is a trademark owned by or licensed to its respective owner and is not a trademark owned by or licensed to the ViiV Healthcare group of companies. The maker of this brand is not affiliated with and does not endorse the ViiV Healthcare group of companies or its products.

©2025 ViiV Healthcare group of companies or its licensor.

VCB:7PIL

For more information call 1-877-844-8872.

This Patient Information has been approved by the U.S. Food and Drug Administration. Revised: 4/2025

PACKAGE LABEL

PRINCIPAL DISPLAY PANEL

NDC 49702-248-13

VOCABRIA

(cabotegravir)

Tablets

30 mg

Rx Only

Note to pharmacist:

Do not cover ALERT box with pharmacy label.

ALERT: Find out about medicines that should NOT be taken with VOCABRIA.

30 tablets

Each tablet contains 30 mg of cabotegravir equivalent to 31.62 mg of cabotegravir sodium.

This package is child-resistant.

Keep out of reach of children.

Store below 30°C (86°F).

Do not accept if safety seal under cap is missing or broken.

See prescribing information for dosage information.

ViiV Healthcare

Mfd for:

ViiV Healthcare

Durham, NC 27701

by:

GlaxoSmithKline

Durham, NC 27701

Trademarks owned or licensed by ViiV Healthcare.

©2023 ViiV Healthcare of licensor.

Made in Singapore

Rev.4/23

A087339 (62000000087339)